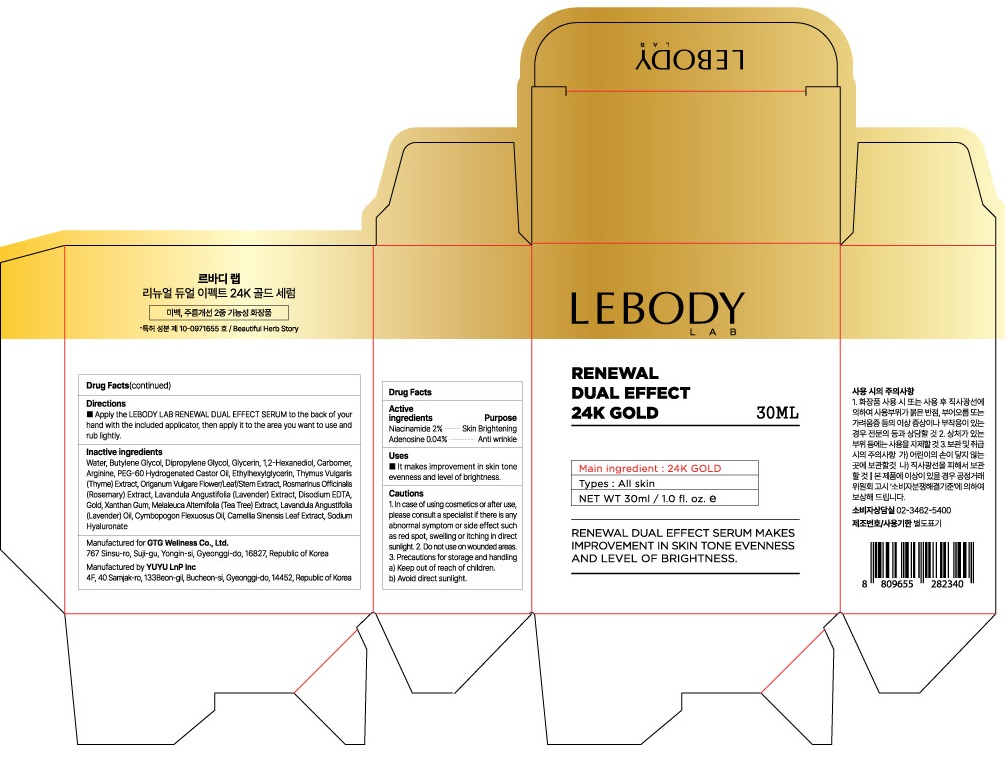 DRUG LABEL: LEBODY LAB RENEWAL DUAL EFFECT 24K GOLD SERUM
NDC: 71080-0011 | Form: LIQUID
Manufacturer: GTG Wellness Co., Ltd.
Category: otc | Type: HUMAN OTC DRUG LABEL
Date: 20230224

ACTIVE INGREDIENTS: Niacinamide 0.6 g/30 mL; Adenosine 0.012 g/30 mL
INACTIVE INGREDIENTS: Water; Glycerin

ACTIVE INGREDIENTS

Niacinamide 2%

Adenosine 0.04%

INACTIVE INGREDIENT

Water, Butylene Glycol, Dipropylene Glycol, Glycerin, 1,2-Hexanediol, Carbomer, Arginine, PEG-60 Hydrogenated Castor Oil, Ethylhexylglycerin, Thymus Vulgaris (Thyme) Extract, Origanum Vulgare Flower/Leaf/Stem Extract, Rosmarinus Officinalis (Rosemary) Extract, Lavandula Angustifolia (Lavender) Extract, Disodium EDTA, Gold, Xanthan Gum, Melaleuca Alternifolia (Tea Tree) Extract, Lavandula Angustifolia (Lavender) Oil, Cymbopogon Flexuosus Oil, Camellia Sinensis Leaf Extract, Sodium Hyaluronate

PURPOSE

Skin Brightening

Anti wrinkle

Cautions

1. In case of using cosmetics or after use, please consult a specialist if there is any abnormal symptom or side effect such as red spot, swelling or itching in direct sunlight.
2. Do not use on wounded areas.
3. Precautions for storage and handling
a) Keep out of reach of children.
b) Avoid direct sunlight.

KEEP OUT OF REACH OF CHILDREN

Uses

■ It makes improvement in skin tone evenness and level of brightness.

Directions

Apply the LEBODY LAB RENEWAL DUAL EFFECT 24K GOLD SERUM to the back of your hand with the included applicator, then apply it to the area you want to use and rub lightly.